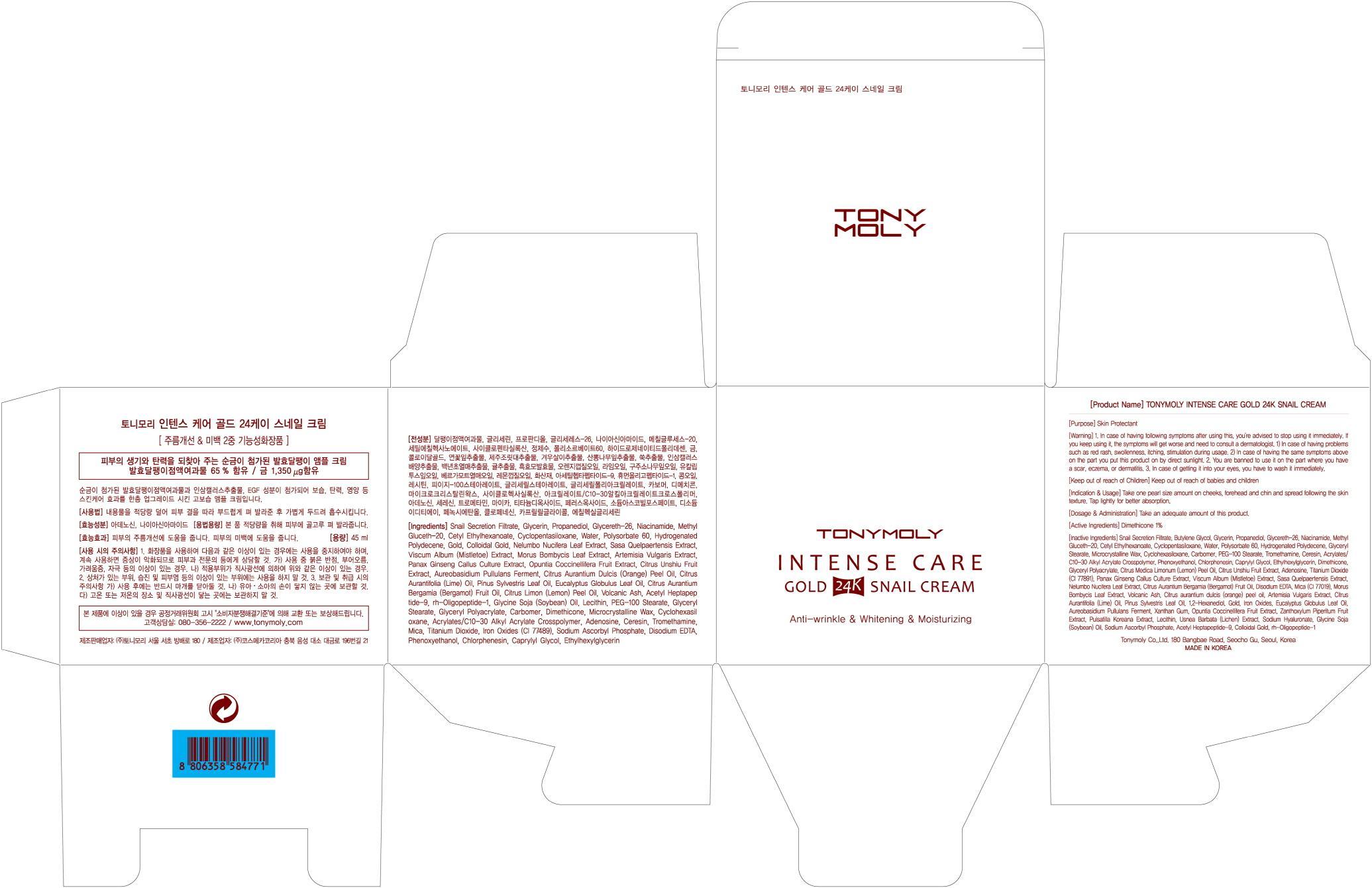 DRUG LABEL: TONYMOLY INTENSE CARE GOLD 24K SNAIL
NDC: 59078-045 | Form: CREAM
Manufacturer: TONYMOLY CO., LTD.
Category: otc | Type: HUMAN OTC DRUG LABEL
Date: 20140625

ACTIVE INGREDIENTS: Dimethicone 0.45 mg/45 mL
INACTIVE INGREDIENTS: Butylene Glycol; Glycerin

ACTIVE INGREDIENT

Active Ingredient: Dimethicone 1%

INACTIVE INGREDIENT

Inactive Ingredients:
Snail Secretion Filtrate, Butylene Glycol, Glycerin, Propanediol, Glycereth-26, Niacinamide, Methyl Gluceth-20, Cetyl Ethylhexanoate, Cyclopentasiloxane, Water, Polysorbate 60, Hydrogenated Polydecene, Glyceryl Stearate, Microcrystalline Wax, Cyclohexasiloxane, Carbomer, PEG-100 Stearate, Tromethamine, Ceresin, Acrylates/C10-30 Alkyl Acrylate Crosspolymer, Phenoxyethanol, Chlorphenesin, Caprylyl Glycol, Ethylhexylglycerin, Dimethicone, Glyceryl Polyacrylate, Citrus Medica Limonum (Lemon) Peel Oil, Citrus Unshiu Fruit Extract, Adenosine, Titanium Dioxide (CI 77891), Panax Ginseng Callus Culture Extract, Viscum Album (Mistletoe) Extract, Sasa Quelpaertensis Extract, Nelumbo Nucifera Leaf Extract, Citrus Aurantium Bergamia (Bergamot) Fruit Oil, Disodium EDTA, Mica (CI 77019), Morus Bombycis Leaf Extract, Volcanic Ash, Citrus aurantium dulcis (orange) peel oil, Artemisia Vulgaris Extract, Citrus Aurantifolia (Lime) Oil, Pinus Sylvestris Leaf Oil, 1,2-Hexanediol, Gold, Iron Oxides, Eucalyptus Globulus Leaf Oil, Aureobasidium Pullulans Ferment, Xanthan Gum, Opuntia Coccinellifera Fruit Extract, Zanthoxylum Piperitum Fruit Extract, Pulsatilla Koreana Extract, Lecithin, Usnea Barbata (Lichen) Extract, Sodium Hyaluronate, Glycine Soja (Soybean) Oil, Sodium Ascorbyl Phosphate, Acetyl Heptapeptide-9, Colloidal Gold, rh-Oligopeptide-1

PURPOSE

Purpose: Skin Protectant

WARNINGS

Warning:
1. In case of having following symptoms after using this, you're advised to stop using it immediately. If you keep using it, the symptoms will get worse and need to consult a dermatologist.
1) In case of having problems such as red rash, swollenness, itching, stimulation during usage.
2) In case of having the same symptoms above on the part you put this product on by direct sunlight.
2. You are banned to use it on the part where you have a scar, eczema, or dermatitis.
3. In case of getting it into your eyes, you have to wash it immediately.

KEEP OUT OF REACH OF CHILDREN

Keep out of reach of babies and children

INDICATIONS AND USAGE

Take one pearl size amount on cheeks, forehead and chin and spread following the skin texture.
Tap lightly for better absorption.

DOSAGE AND ADMINISTRATION

Take an adequate amount of this product.